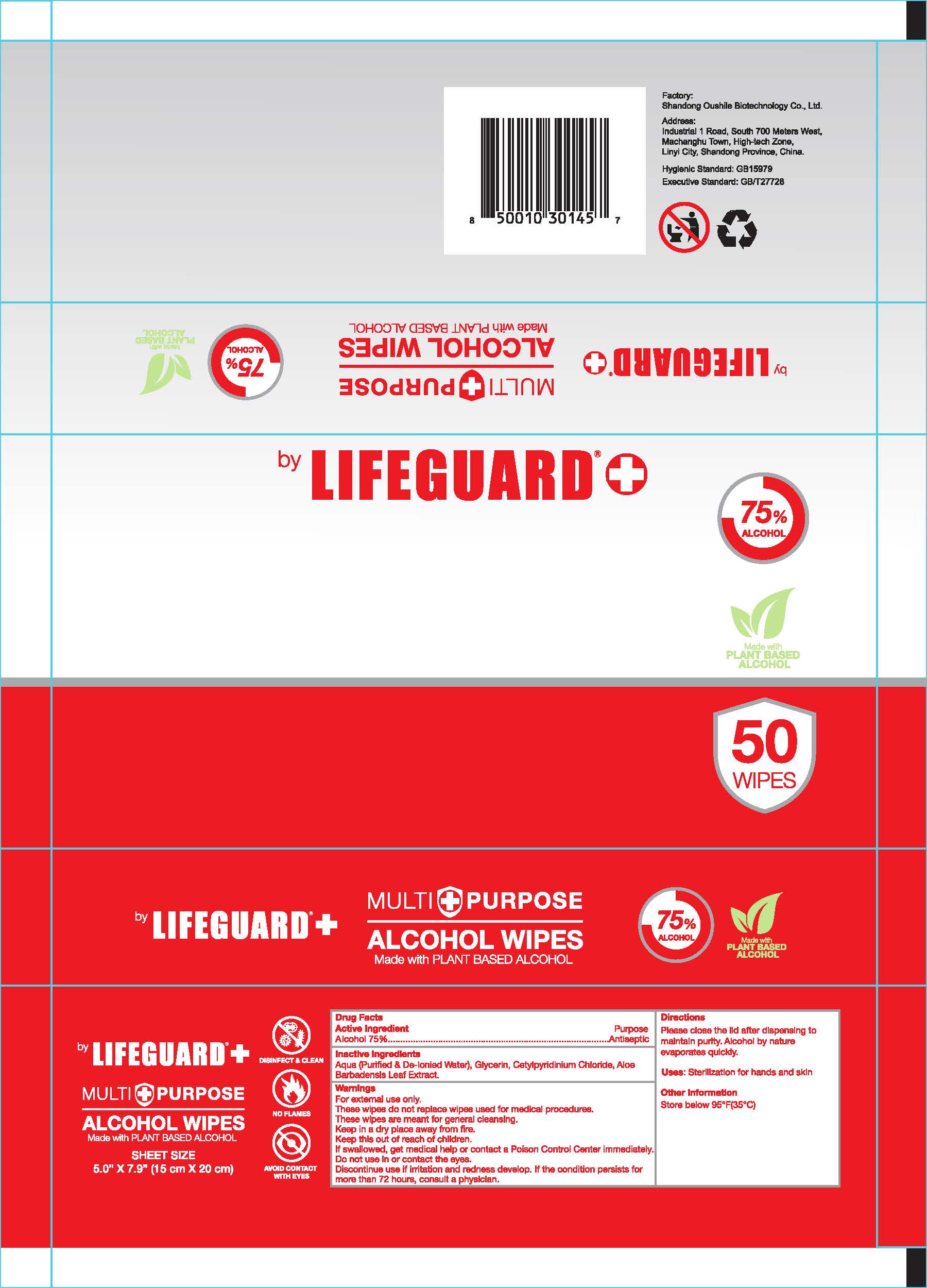 DRUG LABEL: ALCOHOL WIPES
NDC: 78781-006 | Form: CLOTH
Manufacturer: Shandong Oushile Biotechnology Co.Ltd
Category: otc | Type: HUMAN OTC DRUG LABEL
Date: 20200729

ACTIVE INGREDIENTS: ALCOHOL 75 1/100 1
INACTIVE INGREDIENTS: GLYCERIN; CETYLPYRIDINIUM CHLORIDE; WATER; ALOE VERA LEAF

ALCOHOL WIPES

Active Ingredient(s)

Alcohol 75%

Purpose

Antisepticnactive

Use

Sterilization for hands and skin

Warnings

For external use only.
These wipes do not replace wipes used for medical procedures.
These wipes are meant for general cleansing.
Keep in a dry place away from fire.

Do not use in or contact the eyes.

WHEN USING

These wipes are meant for general cleansing.
Keep in a dry place away from fire.

STOP USE

Discontinue use if irritation and redness develop. If the condition persists for more than 72 hours, consult a physician.

Keep this out of reach of children.
If swallowed, get medical help or contact a Poison Control Center immediately.

Directions

Please close the lid after dispensing to maintain purity, Alcohol by nature evaporates quickly.

Other information

Store below 95°F(35°C)

Inactive ingredients

Aqua (Purified& De-lonied Water), Glycerin, Cetylpyridinium Chloride, Aloe Barbadensis leaf extract